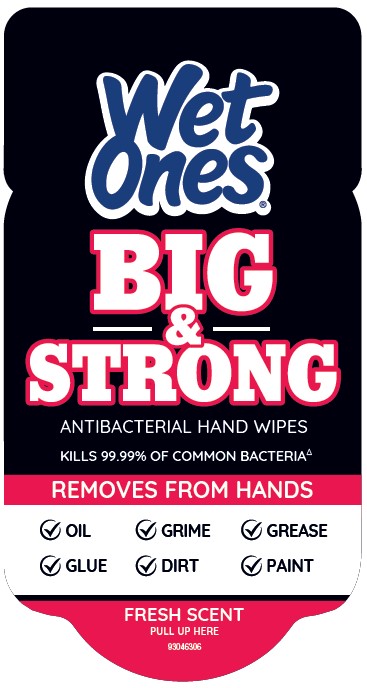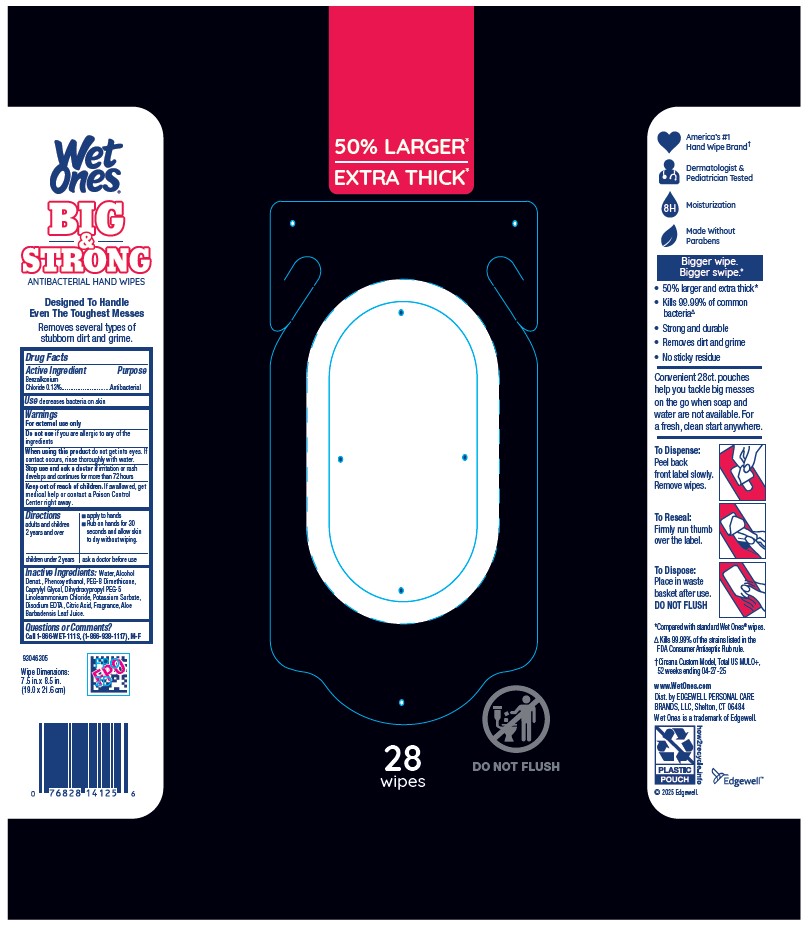 DRUG LABEL: WET ONES
NDC: 63354-772 | Form: SWAB
Manufacturer: Edgewell Personal Care Brands LLC
Category: otc | Type: HUMAN OTC DRUG LABEL
Date: 20250917

ACTIVE INGREDIENTS: BENZALKONIUM CHLORIDE 0.13 g/1 1
INACTIVE INGREDIENTS: CAPRYLYL GLYCOL; PEG-8 DIMETHICONE; ALCOHOL; PHENOXYETHANOL; DIHYDROXYPROPYL PEG-5 LINOLEAMMONIUM CHLORIDE; EDETATE DISODIUM; ALOE VERA LEAF; WATER; POTASSIUM SORBATE; CITRIC ACID MONOHYDRATE

Active Ingredient

Benzalkonium Chloride 0.13%

Purpose

Antibacterial

Use

decreases bacteria on skin

Warnings

For external use only

Do not use

if you are allergic to any of the ingredients

When using this product

do not get into eyes. If contact occurs, rinse thoroughly with water.

Stop use and ask a doctor if

irritation or rash develops and continues for more than 72 hours

Stop use and ask a doctor if

irritation or rash develops and continues for more than 72 hours

Keep out of reach of children.

If swallowed, get medical help or contact a Poison Control Center right away.

Directions

• apply to hands • adults and children 2 years and over: Rub on hands for 30 seconds and allow skin to dry without wiping.

children under 2 years: ask a doctor before use.

Inactive Ingredients

Water, Alcohol Denat., Phenoxyethanol, PEG-8 Dimethicone, Caprylyl Glycol, Dihydroxypropyl PEG-5 Linoleammonium Chloride, Potassium Sorbate, Disodium EDTA, Citric Acid, Fragrance, Aloe Barbadensis Leaf Juice.

Questions or Comments?

Call 1-866-WET-111S, (1-866-938-1117), M-F

Principal Display Panel

Wet
Ones
BIG
&
STRONG
ANTIBACTERIAL HAND WIPE
KILLS 99.99% OF COMMON BACTERIA
REMOVES FROM HANDS
• OIL • GRIME • GREASE
• GLUE • DIRT • PAINT
FRESH SCENT
PULL UP HERE

50% LARGE
EXTRA THICK
28
wipes
DO NOT FLUSH